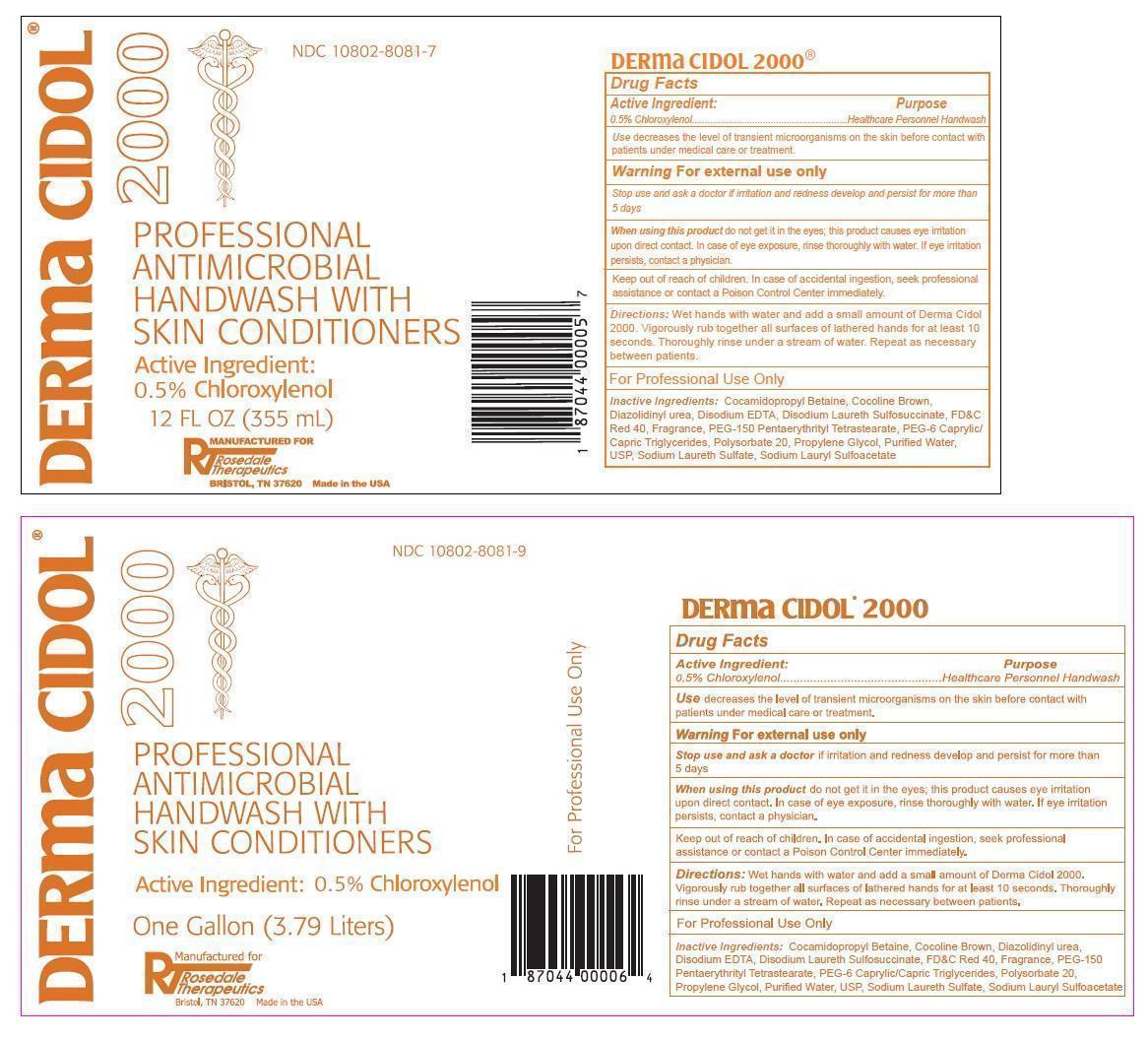 DRUG LABEL: Derma CIDOL 2000
NDC: 10802-8081 | Form: LIQUID
Manufacturer: Rosedale Therapeutics, LLC
Category: otc | Type: HUMAN OTC DRUG LABEL
Date: 20150218

ACTIVE INGREDIENTS: CHLOROXYLENOL 0.5 g/100 mL
INACTIVE INGREDIENTS: COCAMIDOPROPYL BETAINE; FD&C YELLOW NO. 5; FD&C YELLOW NO. 6; FD&C BLUE NO. 1; DIAZOLIDINYL UREA; EDETATE DISODIUM; DISODIUM LAURETH SULFOSUCCINATE; FD&C RED NO. 40; POLYETHYLENE GLYCOL 7000; PENTAERYTHRITYL TETRASTEARATE; PEG-6 CAPRYLIC/CAPRIC GLYCERIDES; POLYSORBATE 20; PROPYLENE GLYCOL; WATER; SODIUM LAURETH-3 SULFATE; SODIUM LAURYL SULFOACETATE

Derma CIDOL 2000

Active Ingredient:

0.5% Chloroxylenol

Purpose

Healthcare Personnel Handwash

Keep out of reach of children. In case of accidental ingestion, seek professional assistance or contact a Poison Control Center immediately.

INDICATIONS AND USAGE

Use decreases the level of transient microorganisms on the skin before contact with patients under medical care or treatment.

Warning For external use only

Stop use and ask a doctor if irritation and redness develop and persist for more than 5 days.

When using this product do not get it in the eyes; this product causes eye irritation upon direct contact. In case of eye exposure, rinse thoroughly with water. If eye irritation persists, contact a physician.

DOSAGE AND ADMINISTRATION

Directions: Wet hands with water and add a small amount of Derma Cidol 2000. Vigorously rub together all surfaces of lathered hands for at least 10 seconds. Thoroughly rinse under a stream of water. Repeat as necessary between patients.

For Professional Use Only

INACTIVE INGREDIENT

Inactive Ingredients: Cocamidopropyl Betaine, Cocoline Brown, Diazolidinyl urea, Disodium EDTA, Disodium Laureth Sulfosuccinate, FD&C Red 40, Fragrance, PEG-150, Pentaerythrityl Tetrastearate, PEG-6 Caprylic/Capric Triglycerides, Polysorbate 20, Propylene Glycol, Purified Water USP, Sodium Laureth Sulfate, Sodium Lauryl Sulfoacetate